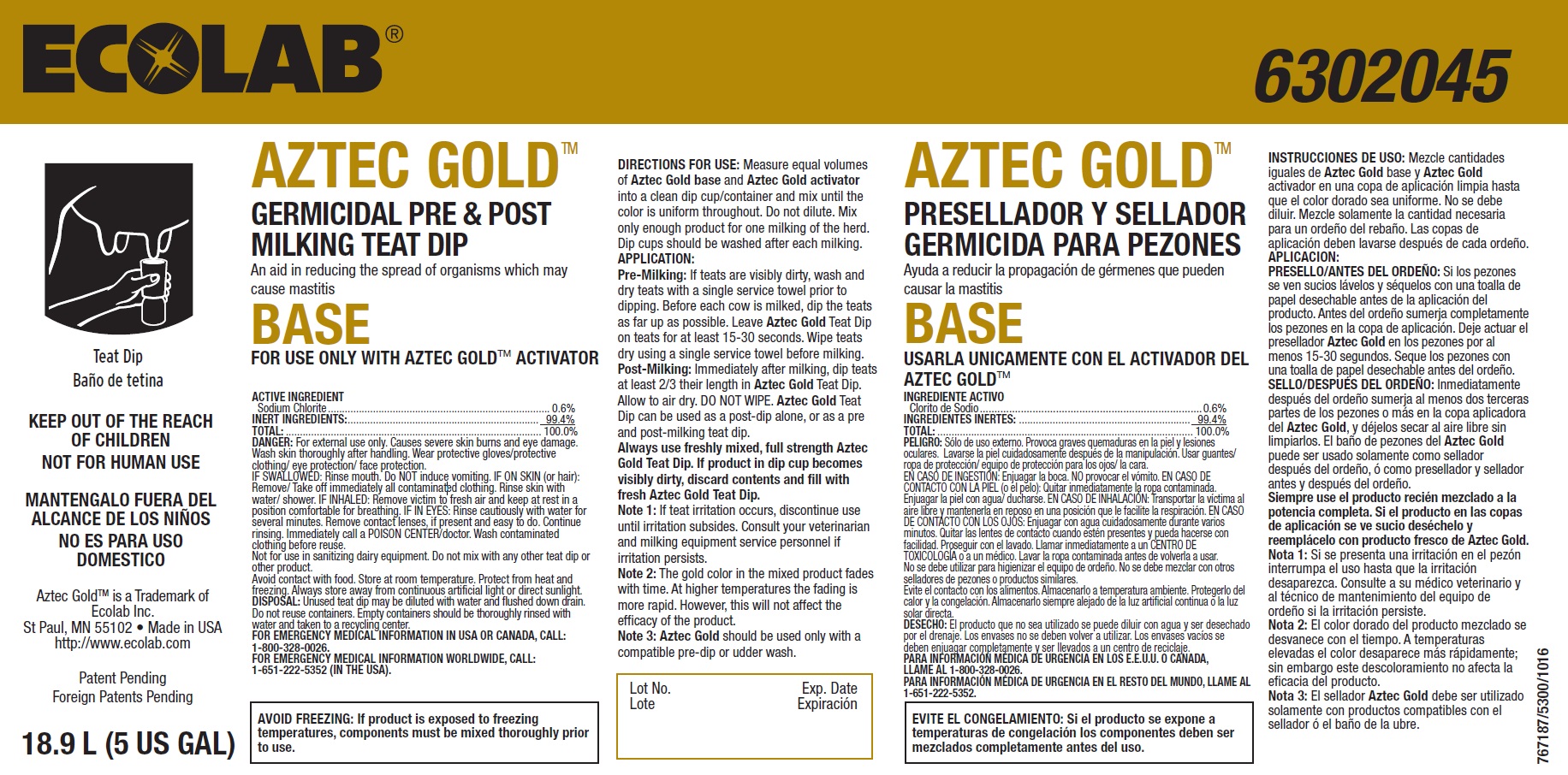 DRUG LABEL: Aztec Gold
NDC: 47593-460 | Form: SOLUTION
Manufacturer: Ecolab Inc.
Category: animal | Type: OTC ANIMAL DRUG LABEL
Date: 20251012

ACTIVE INGREDIENTS: SODIUM CHLORITE 6 mg/1 mL
INACTIVE INGREDIENTS: WATER

SAFE HANDLING WARNING

KEEP OUT OF THE REACH
OF CHILDREN
NOT FOR HUMAN USE

DANGER: For external use only. Causes severe skin burns and eye damage.

Wash skin thoroughly after handling. Wear protective gloves/protective clothing/ eye protection/ face protection.

DISPOSAL: Unused teat dip may be diluted with water and flushed down drain.
Do not reuse containers. Empty containers should be thoroughly rinsed with
water and taken to a recycling center.

AVOID FREEZING: If product is exposed to freezing
temperatures, components must be mixed thoroughly prior
to use.

VETERINARY INDICATIONS

DIRECTIONS FOR USE: Measure equal volumes

of Aztec Gold base and Aztec Gold activator

into a clean dip cup/container and mix until the

color is uniform throughout. Do not dilute. Mix

only enough product for one milking of the herd.

Dip cups should be washed after each milking.

APPLICATION:

Pre-Milking: If teats are visibly dirty, wash and

dry teats with a single service towel prior to

dipping. Before each cow is milked, dip the teats

as far up as possible. Leave Aztec Gold Teat Dip

on teats for at least 15-30 seconds. Wipe teats

dry using a single service towel before milking.

Post-Milking: Immediately after milking, dip teats

at least 2/3 their length in Aztec Gold Teat Dip.

Allow to air dry. DO NOT WIPE. Aztec Gold Teat

Dip can be used as a post-dip alone, or as a pre

and post-milking teat dip.

Always use freshly mixed, full strength Aztec

Gold Teat Dip. If product in dip cup becomes

visibly dirty, discard contents and fill with

fresh Aztec Gold Teat Dip.

Note 1: If teat irritation occurs, discontinue use

until irritation subsides. Consult your veterinarian

and milking equipment service personnel if

irritation persists.

Note 2: The gold color in the mixed product fades

with time. At higher temperatures the fading is

more rapid. However, this will not affect the

efficacy of the product.

Note 3: Aztec Gold should be used only with a

compatible pre-dip or udder wash.

OTHER SAFETY INFORMATION

DANGER: For external use only. Causes severe skin burns and eye damage.

Wash skin thoroughly after handling. Wear protective gloves/protective

clothing/ eye protection/ face protection.

IF SWALLOWED: Rinse mouth. Do NOT induce vomiting. IF ON SKIN (or hair):

Remove/ Take off immediately all contaminated clothing. Rinse skin with

water/ shower. IF INHALED: Remove victim to fresh air and keep at rest in a

position comfortable for breathing. IF IN EYES: Rinse cautiously with water for

several minutes. Remove contact lenses, if present and easy to do. Continue

rinsing. Immediately call a POISON CENTER/doctor. Wash contaminated

clothing before reuse.

Not for use in sanitizing dairy equipment. Do not mix with any other teat dip or

other product.

Avoid contact with food. Store at room temperature. Protect from heat and

freezing. Always store away from continuous artificial light or direct sunlight.

FOR EMERGENCY MEDICAL INFORMATION IN USA OR CANADA, CALL:

1-800-328-0026.

FOR EMERGENCY MEDICAL INFORMATION WORLDWIDE, CALL:

1-651-222-5352 (IN THE USA).

Principal Display Panel and Representative Label

ECOLAB®

AZTEC GOLD™

GERMICIDAL PRE & POST
MILKING TEAT DIP

An aid in reducing the spread of organisms which may
cause mastitis
BASE
FOR USE ONLY WITH AZTEC GOLD™ ACTIVATOR

ACTIVE INGREDIENT

Sodium Chlorite ........................................................... 0.6%

INACTIVE INGREDIENT ............................................ 99.4%

Aztec GoldTM is a Trademark of
Ecolab Inc.
St Paul, MN 55102 • Made in USA
http://www.ecolab.com

Patent Pending
Foreign Patents Pending

18.9L (5 US GAL)